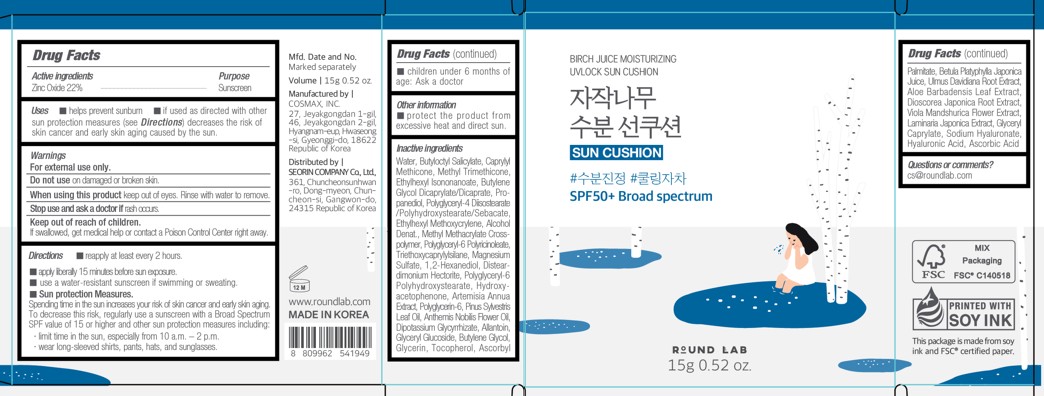 DRUG LABEL: Round Lab Birch Juice Moisturizing UVLOCK Sun Cushion
NDC: 84616-004 | Form: SPONGE
Manufacturer: SEORIN COMPANY Co., Ltd.
Category: otc | Type: HUMAN OTC DRUG LABEL
Date: 20241106

ACTIVE INGREDIENTS: ZINC OXIDE 22.28325 g/100 g
INACTIVE INGREDIENTS: ETHYLHEXYL ISONONANOATE; BUTYLENE GLYCOL DICAPRYLATE/DICAPRATE; BUTYLENE GLYCOL; GLYCERIN; ASCORBIC ACID; POLYGLYCERYL-4 DIISOSTEARATE/POLYHYDROXYSTEARATE/SEBACATE; 1,2-HEXANEDIOL; HYALURONIC ACID; ETHYLHEXYL METHOXYCRYLENE; BUTYLOCTYL SALICYLATE; CAPRYLYL METHICONE; METHYL TRIMETHICONE; LAMINARIA JAPONICA; ANTHEMIS NOBILIS FLOWER OIL; ASCORBYL PALMITATE; BETULA PLATYPHYLLA JAPONICA JUICE; GLYCERYL CAPRYLATE; SODIUM HYALURONATE; METHYL METHACRYLATE/GLYCOL DIMETHACRYLATE CROSSPOLYMER; PINUS SYLVESTRIS LEAF OIL; MAGNESIUM SULFATE; DIPOTASSIUM GLYCYRRHIZATE; ARTEMISIA ANNUA WHOLE; PROPANEDIOL; WATER; TRIETHOXYCAPRYLYLSILANE; DISTEARDIMONIUM HECTORITE; POLYGLYCERIN-6; ALOE VERA LEAF; GLYCERYL GLUCOSIDE; DIOSCOREA JAPONICA ROOT; VIOLA MANDSHURICA FLOWER; TOCOPHEROL; ULMUS DAVIDIANA ROOT; HYDROXYACETOPHENONE; ARTEMISIA ANNUA LEAF; ALLANTOIN; POLYGLYCERYL-6 POLYRICINOLEATE

Round Lab
Birch Juice Moisturizing
UVLOCK Sun Cushion
SPF50+ Broad spectrum

Active Ingredients

Zinc Oxide 22%

Purpose

Sunscreen

Uses

- helps prevent sunburn
- if used as directed with other sun protection measures (see Directions) decreases the risk of skin cancer and early skin aging caused by the sun.

Warnings

For external use only.

Do not use on damaged or broken skin.

When using this product keep out of eyes. Rinse with water to remove

Stop use and ask a doctor if rash occurs

Keep out of reach of children.

OTHER SAFETY INFORMATION

If swallowed, get medical help or contact a Poison Control Center right away.

OTHER SAFETY INFORMATION

If swallowed, get medical help or contact a Poison Control Center right away.

Directions

- reapply at least every 2 hours.
- apply liberally 15 minutes before sun exposure.
- use a water-resistant sunscreen if swimming or sweating.
- Sun protection measures. Spending time in the sun increases your risk of skin cancer and early aging. To decrease this risk, regularly use a sunscreen with a Broad Spectrum SPF value of 15 or higher and other sun protection measures including: limit time in the sun, especially from 10 a.m. - 2 p.m., wear long-sleeved shirts, pants, hats, and sunglasses
- children under 6 months of age: Ask a doctor

Other Information

protect the product from excessive heat and direct sun

Inactive ingredients

Water, Butyloctyl Salicylate, Caprytyl Methicone, Methyl Trimethicone, Ethylhexyl Isononanoate, Butylene Glycol Dicaprylate/Dicaprate, Pro-panecio, Polyglypery -4 Disostearate/Polyhydroxystearate/Sebacate, Ethylhexyl Methoxycrylene, Alcohol Denat., Methyl Methacrylate Cross-polymer, Polyglycery -6 Polyricinoleate, Triethoxycaprylyisilane, Magnesium Sulfate, 1,2- Hexanediol, Distearimonium Hectorite, Polyglyceryl-6 Polyhydroxystearate, Hydroxy-acetophenone, Artemisia Annua Extract, Polyglyperin-6, Pinus Sylvestris Leaf Oil, Anthemis Nobils Flower Oil, Dipotassium Glycyrrhizate, Allantoin, Glyceryl Glucaside, Butyiene Glycol Glycerin, Tocopherol, Ascorbyl Palmitate, Betula Platyphylla Japonica Juice, Umus Davidiana Root Extract, Aloe Barbadensis Leaf Extract, Dioscorea Japonica Root Extract, Viola Mandshurica Flower Extract, Laminaria Japonica Extract, Glyceryl Caprylate, Sodium Hyaluronate Hyaluronic Acid, Ascorbic Acid

Questions or comments?

cs@roundlab.com

PACKAGE LABEL

BIRCH JUICE MOISTURIZING

UVLOCK SUN CUSHION

SUN CUSHION

SPF50+ Broad spectrum

ROUND LAB

15g 0.52 oz.